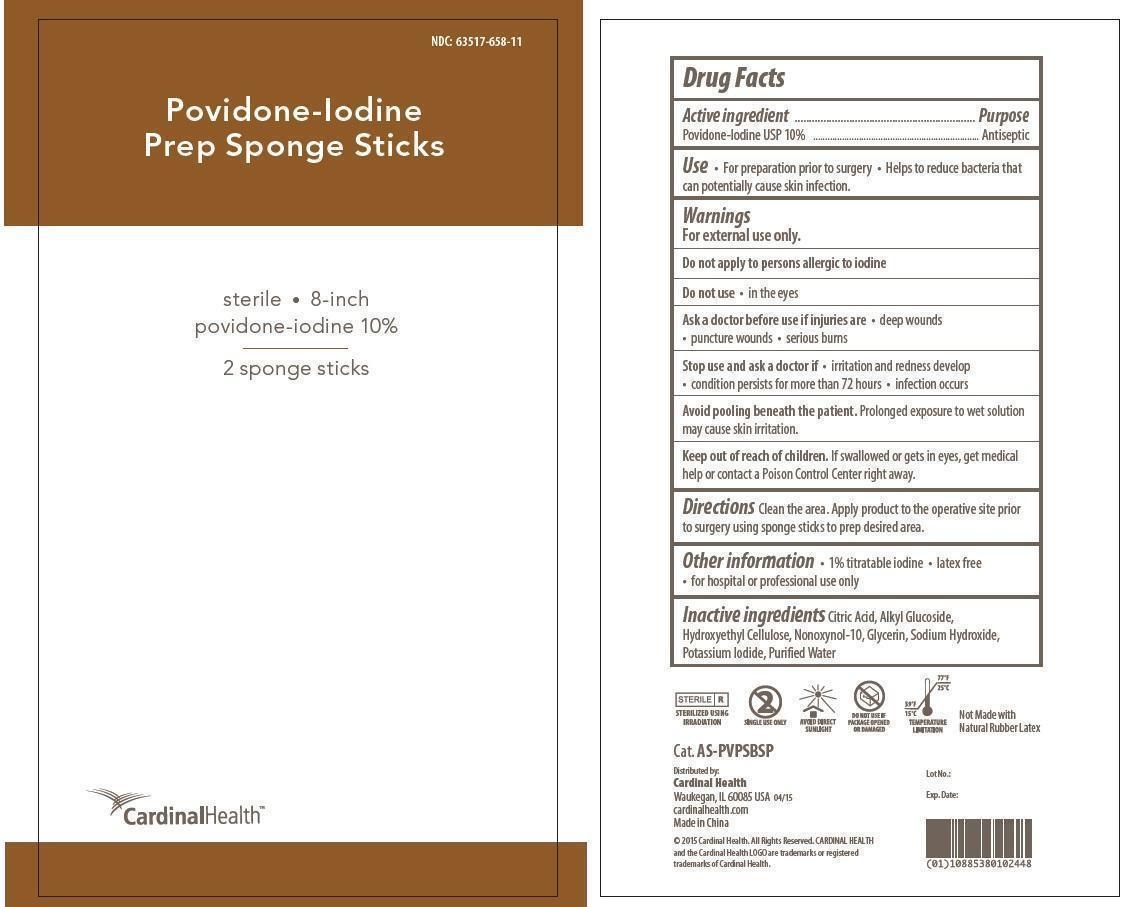 DRUG LABEL: Povidone-Iodine Prep Sterile
NDC: 59050-658 | Form: SPONGE
Manufacturer: Changzhou Maokang Medical Products Co., Ltd
Category: otc | Type: HUMAN OTC DRUG LABEL
Date: 20231213

ACTIVE INGREDIENTS: POVIDONE-IODINE 100 mg/1 g
INACTIVE INGREDIENTS: CITRIC ACID MONOHYDRATE; HYDROXYETHYL CELLULOSE, UNSPECIFIED; NONOXYNOL-10; GLYCERIN; SODIUM HYDROXIDE; POTASSIUM IODIDE; WATER

Povidone-Iodine Prep Sponge Sticks Sterile

Active ingredient

Povidone-Iodine USP 10%

Purpose

Antiseptic

Use

- For preparation prior to surgery
- Helps to reduce bacteria that can potentially cause skin infection.

Warnings

For external use only.

Do not apply to persons allergic to iodine

Do not use

- in the eyes

Ask a doctor before use if

injuries are • deep wounds

• puncture wounds • serious burns

Stop use and ask a doctor if

• irritation and redness develop

• condition persists for more than 72 hours • infection occurs

Avoid pooling beneath the patient.Prolonged exposure to wet solution may cause skin irritation.

Keep out of reach of children.

If swallowed or gets in eyes, get medical help or contact a Poison Control Center right away.

Directions

Clean the area. Apply product to the operative site prior to surgery using sponge sticks to prep desired area.

Other information

• 1% titratable iodine • latex free • for hospital or professional use only

Inactive ingredients

Citric Acid, Alkyl Glucoside, Hydroxyethyl Cellulose, Nonoxynol-10, Glycerin, Sodium Hydroxide, Potassium Iodide, Purified Water